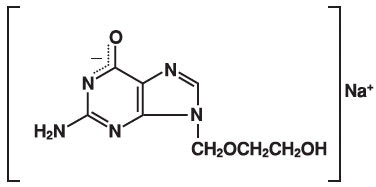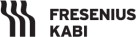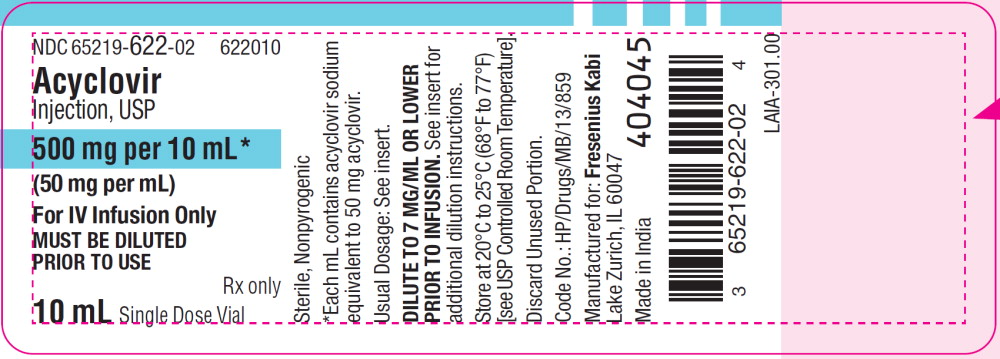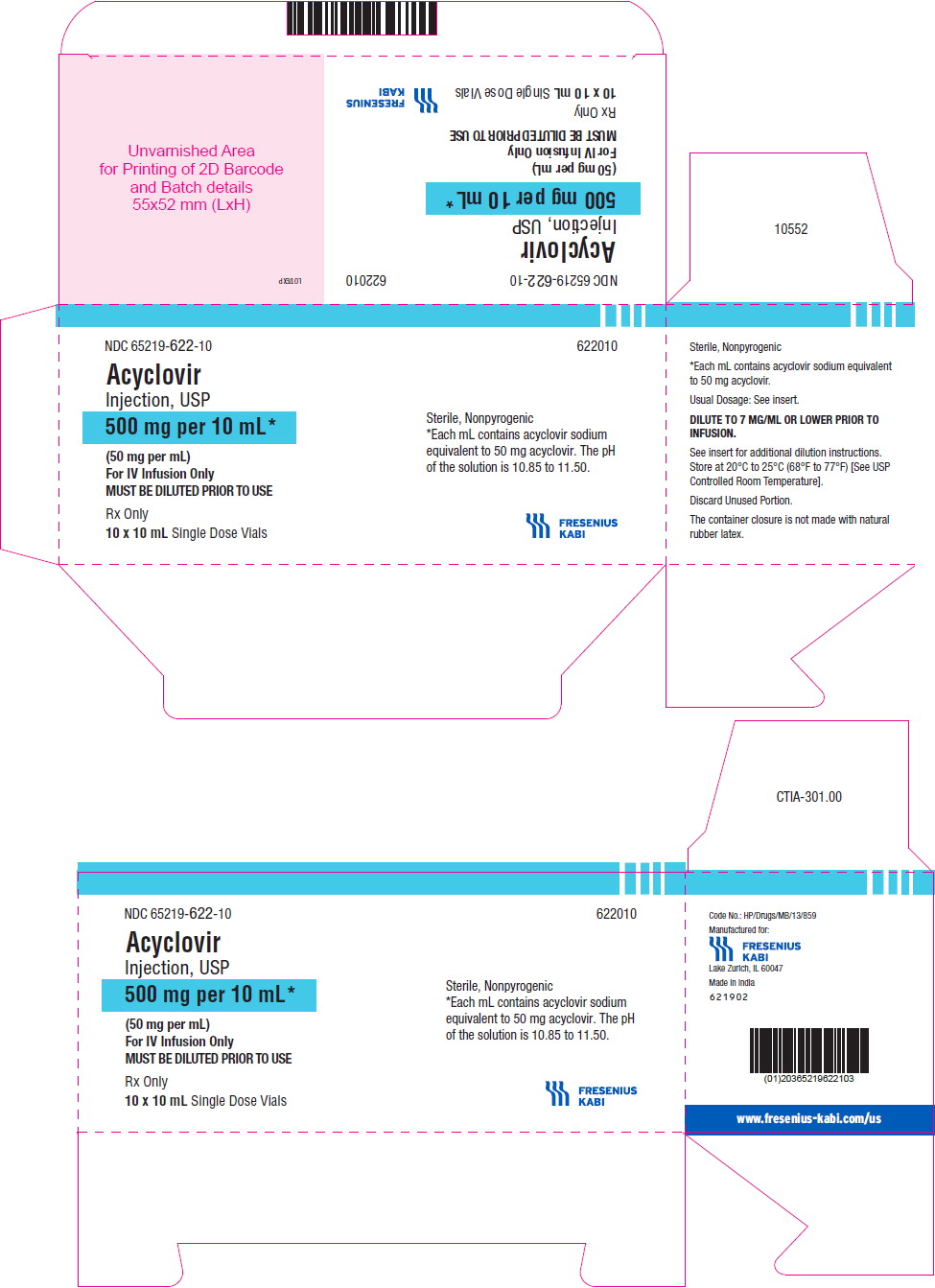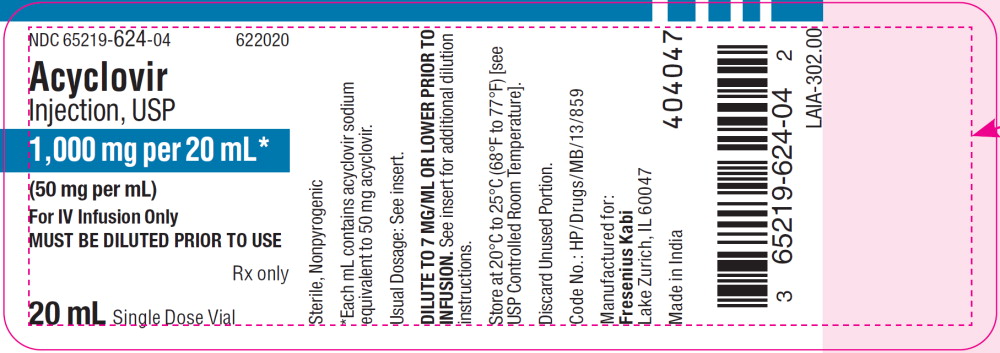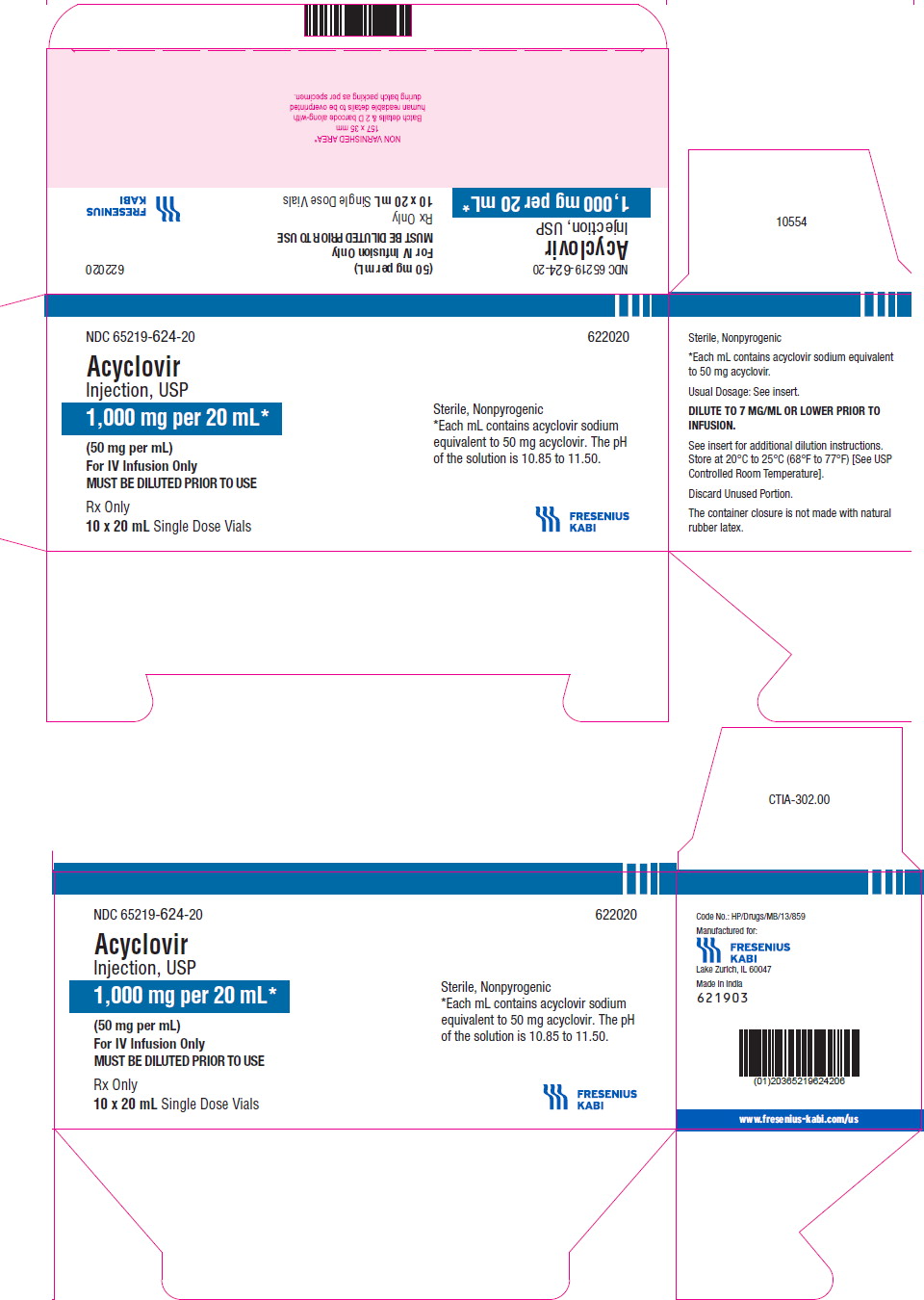 DRUG LABEL: acyclovir
NDC: 65219-622 | Form: INJECTION, SOLUTION
Manufacturer: Fresenius Kabi USA, LLC
Category: prescription | Type: HUMAN PRESCRIPTION DRUG LABEL
Date: 20241113

ACTIVE INGREDIENTS: ACYCLOVIR SODIUM 50 mg/1 mL
INACTIVE INGREDIENTS: WATER; NITROGEN

Acyclovir Injection, USP

FOR INTRAVENOUS INFUSION ONLY

Rx only

DESCRIPTION

Acyclovir Injection, USP is a synthetic nucleoside analog, active against herpes viruses. It is a sterile, aqueous solution for intravenous infusion, containing 50 mg acyclovir per mL in Water for Injection, USP. The concentration is equivalent to 54.9 mg of acyclovir sodium per mL in Water for Injection, USP. The sodium content is approximately 5.1 mg/mL. The pH range of the solution is 10.85 to 11.50. Further dilution of Acyclovir Injection, USP in an appropriate intravenous solution must be performed before infusion (see DOSAGE AND ADMINISTRATION, Administration).

The chemical name of acyclovir sodium is 9-[(2-Hydroxyethoxy)methyl] guanine, and has the following structural formula:

Acyclovir sodium is a white, crystalline powder with the molecular formula C8H10N5NaO3 and a molecular weight of 247.19. The maximum solubility in water at 25°C exceeds 100 mg/mL. At physiologic pH, acyclovir sodium exists as the unionized form with a molecular weight of 225 and a maximum solubility in water at 37°C of 2.5 mg/mL. The pka's of acyclovir are 2.27 and 9.25.

VIROLOGY:

Mechanism of Antiviral Action

Acyclovir is a synthetic purine nucleoside analogue with in vitro and in vivo inhibitory activity against herpes simplex virus types 1 (HSV-1), 2 (HSV-2) and varicella-zoster virus (VZV).

The inhibitory activity of acyclovir is highly selective due to its affinity for the enzyme thymidine kinase (TK) encoded by HSV and VZV. This viral enzyme converts acyclovir into acyclovir monophosphate, a nucleotide analogue. The monophosphate is further converted into diphosphate by cellular guanylate kinase and into triphosphate by a number of cellular enzymes. In vitro, acyclovir triphosphate stops replication of herpes viral DNA. This is accomplished in three ways: 1) competitive inhibition of viral DNA polymerase, 2) incorporation into and termination of the growing viral DNA chain, and 3) inactivation of the viral DNA polymerase. The greater antiviral activity of acyclovir against HSV compared with VZV is due to its more efficient phosphorylation by the viral TK.

Antiviral Activities

The quantitative relationship between the in vitro susceptibility of herpes viruses to antivirals and the clinical response to therapy has not been established in humans, and virus sensitivity testing has not been standardized. Sensitivity testing results, expressed as the concentration of drug required to inhibit by 50% the growth of virus in cell culture (IC50), vary greatly depending upon a number of factors. Using plaque-reduction assays, the IC50 against herpes simplex virus isolates ranges from 0.02 to 13.5 mcg/mL for HSV-1 and from 0.01 to 9.9 mcg/mL for HSV-2. The IC50 for acyclovir against most laboratory strains and clinical isolates of VZV ranges from 0.12 to 10.8 mcg/mL. Acyclovir also demonstrates activity against the Oka vaccine strain of VZV with a mean IC50 of 1.35 mcg/mL.

Drug Resistance

Resistance of HSV and VZV to acyclovir can result from qualitative and quantitative changes in the viral TK and/or DNA polymerase. Clinical isolates of HSV and VZV with reduced susceptibility to acyclovir have been recovered from immunocompromised patients, especially with advanced HIV infection. While most of the acyclovir-resistant mutants isolated thus far from such patients have been found to be TK-deficient mutants, other mutants involving the viral TK gene (TK partial and TK altered) and DNA polymerase have been isolated. TK-negative mutants may cause severe disease in infants and immunocompromised adults. The possibility of viral resistance to acyclovir should be considered in patients who show poor clinical response during therapy.

CLINICAL PHARMACOLOGY:

Pharmacokinetics

The pharmacokinetics of acyclovir after intravenous administration have been evaluated in adult patients with normal renal function during Phase 1/2 studies after single doses ranging from 0.5 to 15 mg/kg and after multiple doses ranging from 2.5 to 15 mg/kg every 8 hours. Proportionality between dose and plasma levels is seen after single doses or at steady-state after multiple dosing. Average steady-state peak and trough concentrations from 1-hour infusions administered every 8 hours are given in Table 1.

Table 1: Acyclovir Peak and Trough Concentrations at Steady-State
Dosage Regimen | CSSmax | CSStrough
5 mg/kg q 8 h (n=8) | 9.8 mcg/mL range: 5.5 to 13.8 | 0.7 mcg/mL range: 0.2 to 1
10 mg/kg q 8 h (n=7) | 22.9 mcg/mL range: 14.1 to 44.1 | 1.9 mcg/mL range: 0.5 to 2.9

Concentrations achieved in the cerebrospinal fluid are approximately 50% of plasma values. Plasma protein binding is relatively low (9% to 33%) and drug interactions involving binding site displacement are not anticipated.

Renal excretion of unchanged drug is the major route of acyclovir elimination accounting for 62% to 91% of the dose. The only major urinary metabolite detected is 9-carboxymethoxymethylguanine accounting for up to 14.1% of the dose in patients with normal renal function.

The half-life and total body clearance of acyclovir are dependent on renal function as shown in Table 2.

Table 2: Acyclovir Half-life and Total Body Clearance
Creatinine Clearance (mL/min/1.73 m^2) |  | Total Body Clearance
Creatinine Clearance (mL/min/1.73 m^2) | Half-Life (hr) | (mL/min/1.73 m^2) | (mL/min/kg)
>80 50 to 80 15 to 50 0 (Anuric) | 2.5 3 3.5 19.5 | 327 248 190 29 | 5.1 3.9 3.4 0.5

Special Populations

Adults with Impaired Renal Function

Acyclovir was administered at a dose of 2.5 mg/kg to 6 adult patients with severe renal failure. The peak and trough plasma levels during the 47 hours preceding hemodialysis were 8.5 mcg/mL and 0.7 mcg/mL, respectively.

Consult DOSAGE AND ADMINISTRATION section for recommended adjustments in dosing based upon creatinine clearance.

Pediatrics

Acyclovir pharmacokinetics were determined in 16 pediatric patients with normal renal function ranging in age from 3 months to 16 years at doses of approximately 10 mg/kg and 20 mg/kg every 8 hours (Table 3). Concentrations achieved at these regimens are similar to those in adults receiving 5 mg/kg and 10 mg/kg every 8 hours, respectively (Table 1). Acyclovir pharmacokinetics were determined in 12 patients ranging in age from birth to 3 months at doses of 5 mg/kg, 10 mg/kg, and 15 mg/kg every 8 hours (Table 3).

Table 3: Acyclovir Pharmacokinetics in Pediatric Patients (Mean ± SD)
Parameter | Aged from Birth to 3 Months (n=12) | Aged 3 Months to 12 Years (n=16)
CL (mL/min/kg) | 4.46 ± 1.61 | 8.44 ± 2.92
VDSS (L/kg) | 1.08 ± 0.35 | 1.01 ± 0.28
Elimination half-life (hours) | 3.8 ± 1.19 | 2.36 ± 0.97

Acyclovir pharmacokinetic samples were collected in full-term and pre-term neonates with normal renal function who received varying dosing regimens of acyclovir for the treatment of suspected neonatal HSV infection. Model-predicted pharmacokinetic parameters stratified by post-menstrual age (PMA) are summarized in Table 4.

Table 4: Acyclovir Pharmacokinetics in Neonates Aged from Birth to 3 Months
Post-Menstrual Age (PMA) | n | IV Dosea | Parameter (Median [Range])
Post-Menstrual Age (PMA) | n | IV Dosea | Cminss (mg/L) | Cmaxss (mg/L) | CL (L/h/kg) | V (L/kg)
<30 Weeks | 13 | 500 mg/m^2 every 8 h or 10 or 20 mg/kg every 12 h | 3.92 (2.38 - 39.3) | 10.3 (4.59 - 110) | 0.21 (0.10 - 0.31) | 2.88 (0.65 - 5.30)
30 to <36 Weeks | 9 | 500 mg/m^2 every 8 h or 10 or 20 mg/kg every 12 h or 20 mg/kg every 8 h | 5.10 (2.54 - 9.62) | 8.83 (5.44 - 29.8) | 0.45 (0.30 - 0.81) | 4.49 (1.87 - 10.85)
36 to 41 Weeks | 6 | 500 mg/m^2 every 8 h | 2.90 (2.19 - 7.46) | 12.4 (10.8 - 86.1) | 0.59 (0.13 - 0.77) | 2.55 (0.29 - 4.09)
Overall | 28 | – | 4.15 (2.19 - 39.3) | 11.1 (4.59 - 110) | 0.28 (0.10 - 0.81) | 3.34 (0.29 - 10.9)
a Administered over 1 hour.

Geriatrics

Acyclovir plasma concentrations are higher in geriatric patients compared with younger adults, in part due to age-related changes in renal function. Dosage reduction may be required in geriatric patients with underlying renal impairment (see PRECAUTIONS, Geriatric Use).

Drug Interactions

Coadministration of probenecid with acyclovir has been shown to increase the mean acyclovir half-life and the area under the concentration-time curve. Urinary excretion and renal clearance were correspondingly reduced.

CLINICAL TRIALS:

Herpes Simplex Infections in Immunocompromised Patients

A multicenter trial of acyclovir at a dose of 250 mg/m^2 every 8 hours (750 mg/m^2/day) for 7 days was conducted in 98 immunocompromised patients (73 adults and 25 children) with orofacial, esophageal, genital and other localized infections (52 treated with acyclovir and 46 with placebo). Acyclovir decreased virus excretion, reduced pain, and promoted healing of lesions.

Initial Episodes of Herpes Genitalis

In placebo-controlled trials, 58 patients with initial genital herpes were treated with intravenous acyclovir 5 mg/kg or placebo (27 patients treated with acyclovir and 31 treated with placebo) every 8 hours for 5 days. Acyclovir decreased the duration of viral excretion, new lesion formation, and duration of vesicles, and promoted healing of lesions.

Herpes Simplex Encephalitis

Sixty-two patients aged 6 months to 79 years with brain biopsy-proven herpes simplex encephalitis were randomized to receive either acyclovir (10 mg/kg every 8 hours) or vidarabine (15 mg/kg/day) for 10 days (28 were treated with acyclovir and 34 with vidarabine). Overall mortality at 12 months for patients treated with acyclovir was 25% compared with 59% for patients treated with vidarabine. The proportion of patients treated with acyclovir functioning normally or with only mild sequelae (e.g., decreased attention span) was 32% compared with 12% of patients treated with vidarabine.

Patients younger than 30 years and those who had the least severe neurologic involvement at time of entry into study had the best outcome with treatment with acyclovir. An additional controlled study performed in Europe demonstrated similar findings.

Neonatal Herpes Simplex Virus Infection

The safety and efficacy of acyclovir was evaluated for the treatment of herpes simplex virus infection in neonates and infants. In one study (Study 1), acyclovir 10 mg/kg every 8 hours (30 mg/kg/day) was compared with vidarabine. In a follow-up study, (Study 2), acyclovir 20 mg/kg every 8 hours (60 mg/kg/day) was compared with acyclovir 15 mg/kg every 8 hours (45 mg/kg/day).

Study 2 was an open-label clinical trial with an objective of establishing the safety and efficacy of acyclovir 15 mg/kg every 8 hours (45 mg/kg/day) or 20 mg/kg every 8 hours (60 mg/kg/day) administered to neonates ≤28 days old with suspected HSV infection. Neonates aged ≤28 days with suspected HSV infection were eligible for enrollment. In total, 88 neonates were enrolled in the trial and received IV acyclovir for 21 days. Of the 88 subjects, 69 had confirmed systemic disease, 10 had confirmed localized disease, and 9 had suspected but unconfirmed infection. Among the 79 subjects with confirmed infection, 13 subjects received 45 mg/kg/day and 66 subjects received 60 mg/kg/day. The mean gestational ages (GA) were 37.5 and 37.9 weeks for the 45-mg/kg/day and 60-mg/kg/day doses, respectively. The number of premature infants (≤37 weeks GA) receiving 45 mg/kg/day and 60 mg/kg/day were 7 (54%) and 22 (33%), respectively.

Among 69 patients with proven systemic (disseminated or CNS) herpes infection, 57 were randomized to receive acyclovir (20 mg/kg every 8 hours) while the remaining 12 patients received a lower dose of acyclovir every 8 hours. Overall, the mortality among patients treated with acyclovir 20 mg/kg every 8 hours was lower compared with patients who received a lower dose of acyclovir.

Varicella-Zoster Infections in Immunocompromised Patients

A multicenter trial of acyclovir at a dose of 500 mg/m^2 every 8 hours for 7 days was conducted in immunocompromised patients with zoster infections (shingles). Ninety-four (94) patients were evaluated (52 patients were treated with acyclovir and 42 with placebo). Acyclovir was superior to placebo as measured by reductions in cutaneous dissemination and visceral dissemination.

INDICATIONS AND USAGE:

Herpes Simplex Infections in Immunocompromised Patients

Acyclovir Injection is indicated for the treatment of initial and recurrent mucosal and cutaneous herpes simplex (HSV-1 and HSV-2) in immunocompromised patients.

Initial Episodes of Herpes Genitalis

Acyclovir Injection is indicated for the treatment of severe initial clinical episodes of herpes genitalis in immuno-competent patients.

Herpes Simplex Encephalitis

Acyclovir Injection is indicated for the treatment of herpes simplex encephalitis.

Neonatal Herpes Simplex Virus Infection

Acyclovir Injection is indicated for the treatment of neonates and infants with herpes simplex infections.

Varicella-Zoster Infections in Immunocompromised Patients

Acyclovir Injection is indicated for the treatment of varicella-zoster (shingles) infections in immunocompromised patients.

CONTRAINDICATIONS:

Acyclovir Injection is contraindicated for patients who develop hypersensitivity to acyclovir or valacyclovir.

WARNINGS:

Acyclovir Injection is intended for intravenous infusion only, and should not be administered topically, intramuscularly, orally, subcutaneously, or in the eye. Intravenous infusions must be given over a period of at least 1 hour to reduce the risk of renal tubular damage (see PRECAUTIONS and DOSAGE AND ADMINISTRATION).

Renal failure, in some cases resulting in death, has been observed with acyclovir therapy (see ADVERSE REACTIONS, Observed During Clinical Practice and OVERDOSAGE). Thrombotic thrombocytopenic purpura/ hemolytic uremic syndrome (TTP/HUS), which has resulted in death, has occurred in immunocompromised patients receiving acyclovir therapy.

PRECAUTIONS:

General

Precipitation of acyclovir crystals in renal tubules can occur if the maximum solubility of free acyclovir (2.5 mg/mL at 37°C in water) is exceeded or if the drug is administered by bolus injection. Ensuing renal tubular damage can produce acute renal failure.

Abnormal renal function (decreased creatinine clearance) can occur as a result of acyclovir administration and depends on the state of the patient's hydration, other treatments, and the rate of drug administration. Concomitant use of other nephrotoxic drugs, pre-existing renal disease, and dehydration make further renal impairment with acyclovir more likely.

Administration of acyclovir by intravenous infusion must be accompanied by adequate hydration.

When dosage adjustments are required, they should be based on estimated creatinine clearance (see DOSAGE AND ADMINISTRATION).

Approximately 1% of patients receiving intravenous acyclovir have manifested encephalopathic changes characterized by either lethargy, obtundation, tremors, confusion, hallucinations, agitation, seizures, or coma. Acyclovir should be used with caution in those patients who have underlying neurologic abnormalities and those with serious renal, hepatic, or electrolyte abnormalities, or significant hypoxia.

Drug Interactions

See CLINICAL PHARMACOLOGY, Pharmacokinetics.

Carcinogenesis, Mutagenesis, Impairment of Fertility

The data presented below include references to peak steady-state plasma acyclovir concentrations observed in humans treated with 30 mg/kg/day (10 mg/kg every 8 hours, dosing appropriate for treatment of herpes zoster or herpes encephalitis), or 15 mg/kg/day (5 mg/kg every 8 hours, dosing appropriate for treatment of primary genital herpes or herpes simplex infections in immunocompromised patients). Plasma drug concentrations in animal studies are expressed as multiples of human exposure to acyclovir at the higher and lower dosing schedules (see CLINICAL PHARMACOLOGY, Pharmacokinetics).

Acyclovir was tested in lifetime bioassays in rats and mice at single daily doses of up to 450 mg/kg administered by gavage. There was no statistically significant difference in the incidence of tumors between treated and control animals, nor did acyclovir shorten the latency of tumors. At 450 mg/kg/day, plasma concentrations in both the mouse and rat bioassay were lower than concentrations in humans.

Acyclovir was tested in 16 in vitro and in vivo genetic toxicity assays. Acyclovir was positive in 5 of the assays.

Acyclovir did not impair fertility or reproduction in mice (450 mg/kg/day, PO) or in rats (25 mg/kg/day, SC). In the mouse study, plasma levels were the same as human levels, while in the rat study, they were 1 to 2 times human levels. At higher doses (50 mg/kg/day, SC) in rats and rabbits (1 to 2 and 1 to 3 times human levels, respectively) implantation efficacy, but not litter size, was decreased. In a rat peri- and post-natal study at 50 mg/kg/day, SC, there was a statistically significant decrease in group mean numbers of corpora lutea, total implantation sites, and live fetuses.

No testicular abnormalities were seen in dogs given 50 mg/kg/day, IV for 1 month (1 to 3 times human levels) or in dogs given 60 mg/kg/day orally for 1 year (the same as human levels). Testicular atrophy and aspermatogenesis were observed in rats and dogs at higher dose levels.

Pregnancy

Teratogenic Effects

Acyclovir administered during organogenesis was not teratogenic in the mouse (450 mg/kg/day, PO), rabbit (50 mg/kg/day, SC and IV) or rat (50 mg/kg/day, SC). These exposures resulted in plasma levels the same as, 4 and 9, and 1 and 2 times, respectively, human levels.

There are no adequate and well-controlled studies in pregnant women. A prospective epidemiologic registry of acyclovir use during pregnancy was established in 1984 and completed in April 1999. There were 749 pregnancies followed in women exposed to systemic acyclovir during the first trimester of pregnancy resulting in 756 outcomes. The occurrence rate of birth defects approximated that found in the general population. However, the small size of the registry was insufficient to evaluate the risk for less common defects or to permit reliable or definitive conclusions regarding the safety of acyclovir in pregnant women and their developing fetuses. Acyclovir should be used during pregnancy only if the potential benefit justifies the potential risk to the fetus.

Nursing Mothers

Acyclovir concentrations have been documented in breast milk in two women following oral administration of acyclovir and ranged from 0.6 to 4.1 times corresponding plasma levels. These concentrations would potentially expose the nursing infant to a dose of acyclovir up to 0.3 mg/kg/day. Acyclovir should be administered to a nursing mother with caution and only when indicated.

Pediatric Use

The safety and efficacy of Acyclovir Injection has been evaluated in pediatric patients, including neonates (see CLINICAL PHARMACOLOGY, CLINICAL TRIALS, INDICATIONS AND USAGE, ADVERSE REACTIONS and DOSAGE AND ADMINISTRATION).

Geriatric Use

Clinical studies of Acyclovir Injection did not include sufficient numbers of patients aged 65 and older to determine whether they respond differently from younger patients. Other reported clinical experience has identified differences in the severity of CNS adverse events between elderly and younger patients (see ADVERSE REACTIONS, Observed During Clinical Practice). In general, dose selection for an elderly patient should be cautious, reflecting the greater frequency of decreased renal function, and of concomitant disease or other drug therapy. This drug is known to be substantially excreted by the kidney, and the risk of toxic reactions to this drug may be greater in patients with impaired renal function. Because elderly patients are more likely to have decreased renal function, care should be taken in dose selection, and it may be useful to monitor renal function.

ADVERSE REACTIONS:

To report SUSPECTED ADVERSE REACTIONS, contact Fresenius Kabi USA, LLC at 1-800-551-7176 or FDA at 1-800-FDA-1088 or www.fda.gov/medwatch.

Adult and Pediatric Clinical Trials

The adverse reactions listed below have been observed in controlled and uncontrolled clinical trials in approximately 700 patients who received acyclovir at approximately 5 mg/kg (250 mg/m^2) 3 times daily, and approximately 300 patients who received approximately 10 mg/kg (500 mg/m^2) 3 times daily.

The most frequent adverse reactions reported during administration of acyclovir were inflammation or phlebitis at the injection site in approximately 9% of the patients, and transient elevations of serum creatinine or BUN in 5% to 10% (the higher incidence occurred usually following rapid [less than 10 minutes] intravenous infusion). Nausea and/or vomiting occurred in approximately 7% of the patients (the majority occurring in non-hospitalized patients who received 10 mg/kg). Itching, rash, or hives occurred in approximately 2% of patients. Elevation of transaminases occurred in 1% to 2% of patients.

The following hematologic abnormalities occurred at a frequency of less than 1%: anemia, neutropenia, thrombocytopenia, thrombocytosis, leukocytosis, and neutrophilia. In addition, anorexia and hematuria were observed.

Neonatal Clinical Trial

In Study 2, 72 of the 88 enrolled neonates received 60 mg/kg/day. Among subjects with recorded normal baseline values, the following laboratory abnormalities were reported: 6% (4/64) with Grade 3 or 4 increase in creatinine; 4% (2/52) with total bilirubin Grade 3 or 4 toxicity; 13% (8/64) with hemoglobin <8 gram%; 16% (10/64) and 3% (2/64) with absolute neutrophil count 500 to 1,000 cells/mm^3 and <500 cells/mm^3, respectively; 10% (6/63) and 5% (3/63) with platelet count 50,000 to 100,000 and <50,000, respectively.

Observed During Clinical Practice

In addition to adverse events reported from clinical trials, the following events have been identified during post-approval use of Acyclovir Injection in clinical practice. Because they are reported voluntarily from a population of unknown size, estimates of frequency cannot be made. These events have been chosen for inclusion due to either their seriousness, frequency of reporting, potential causal connection to acyclovir, or a combination of these factors.

General: Anaphylaxis, angioedema, fatigue, fever, headache, pain, peripheral edema.

Digestive: Abdominal pain, diarrhea, gastrointestinal distress, nausea.

Cardiovascular: Hypotension.

Hematologic and Lymphatic: Disseminated intravascular coagulation, hemolysis, leukocytoclastic vasculitis, leukopenia, lymphadenopathy.

Hepatobiliary Tract and Pancreas: Elevated liver function tests, hepatitis, hyperbilirubinemia, jaundice.

Musculoskeletal: Myalgia.

Nervous: Aggressive behavior, agitation, ataxia, coma, confusion, delirium, dizziness, dysarthria, encephalopathy, hallucinations, obtundation, paresthesia, psychosis, seizure, somnolence, tremor. These symptoms may be marked, particularly in older adults (see PRECAUTIONS).

Skin: Alopecia, erythema multiforme, photosensitive rash, pruritus, rash, Stevens-Johnson syndrome, toxic epidermal necrolysis, urticaria. Severe local inflammatory reactions, including tissue necrosis, have occurred following infusion of acyclovir into extravascular tissues.

Special Senses: Visual abnormalities.

Urogenital: Renal failure, elevated blood urea nitrogen, elevated creatinine (see WARNINGS).

OVERDOSAGE:

Overdoses involving ingestions of up to 20 g have been reported. Adverse events that have been reported in association with overdosage include agitation, coma, seizures, and lethargy. Precipitation of acyclovir in renal tubules may occur when the solubility (2.5 mg/mL) is exceeded in the intratubular fluid. Overdosage has been reported following bolus injections or inappropriately high doses, and in patients whose fluid and electrolyte balance were not properly monitored. This has resulted in elevated BUN and serum creatinine, and subsequent renal failure. In the event of acute renal failure and anuria, the patient may benefit from hemodialysis until renal function is restored (see DOSAGE AND ADMINISTRATION).

DOSAGE AND ADMINISTRATION:

CAUTION - RAPID OR BOLUS INTRAVENOUS INJECTION MUST BE AVOIDED (see WARNINGS and PRECAUTIONS).

INTRAMUSCULAR OR SUBCUTANEOUS INJECTION MUST BE AVOIDED (see WARNINGS).

Therapy should be initiated as early as possible following onset of signs and symptoms of herpes infections.

A maximum dose equivalent to 20 mg/kg every 8 hours should not be exceeded for any patient.

Dosage

1. HERPES SIMPLEX INFECTIONS
  MUCOSAL AND CUTANEOUS HERPES SIMPLEX (HSV-1 and HSV-2) INFECTIONS IN IMMUNOCOMPROMISED PATIENTS:
  - Adults and Adolescents (Aged 12 years and older):
    5 mg/kg infused at a constant rate over 1 hour, every 8 hours for 7 days.
  - Pediatrics (Aged 3 months to 12 years):
    10 mg/kg infused at a constant rate over 1 hour, every 8 hours for 7 days.
2. SEVERE INITIAL CLINICAL EPISODES OF HERPES GENITALIS:
  - Adults and Adolescents (Aged 12 years and older):
    5 mg/kg infused at a constant rate over 1 hour, every 8 hours for 5 days.
3. HERPES SIMPLEX ENCEPHALITIS:
  - Adults and Adolescents (Aged 12 years and older):
    10 mg/kg infused at a constant rate over 1 hour, every 8 hours for 10 days.
  - Pediatrics (Aged 3 months to 12 years):
    20 mg/kg infused at a constant rate over 1 hour, every 8 hours for 10 days.
4. NEONATAL HERPES SIMPLEX VIRUS INFECTIONS:
  - PMA of at Least 34 Weeks:
    20 mg/kg infused at a constant rate over 1 hour, every 8 hours for 21 days.
  - PMA of Less than 34 Weeks:
    20 mg/kg infused at a constant rate over 1 hour, every 12 hours for 21 days.
    In neonates with ongoing medical conditions affecting their renal function beyond the effect of prematurity, the doses recommended should be used with caution.
5. VARICELLA-ZOSTER INFECTIONS
  ZOSTER IN IMMUNOCOMPROMISED PATIENTS:
  - Adults and Adolescents (Aged 12 years and older):
    10 mg/kg infused at a constant rate over 1 hour, every 8 hours for 7 days.
  - Pediatrics (Younger than 12 years):
    20 mg/kg infused at a constant rate over 1 hour, every 8 hours for 7 days.
  - Obese Patients:
    Obese patients should be dosed at the recommended adult dose using Ideal Body Weight.
6. PATIENTS WITH ACUTE OR CHRONIC RENAL IMPAIRMENT (Older than 3 Months): Refer to DOSAGE AND ADMINISTRATION section for recommended doses, and adjust the dosing interval as indicated in Table 5.

Table 5: Dosage Adjustments for Patients with Renal Impairment
Creatinine Clearance (mL/min/1.73 m^2) | Percent of Recommended Dose | Dosing Interval (hours)
>50 >25 to 50 >10 to 25 ≤10 | 100% 100% 100% 50% | 8 12 24 24

Hemodialysis

For patients who require dialysis, the mean plasma half-life of acyclovir during hemodialysis is approximately 5 hours. This results in a 60% decrease in plasma concentrations following a six-hour dialysis period. Therefore, the patient's dosing schedule should be adjusted so that an additional dose is administered after each dialysis.

Peritoneal Dialysis

No supplemental dose appears to be necessary after adjustment of the dosing interval.

Administration

The calculated dose should then be removed and added to any appropriate intravenous solution at a volume selected for administration during each 1 hour infusion. Infusion concentrations of approximately 7 mg/mL or lower are recommended. In clinical studies, the average 70 kg adult received between 60 and 150 mL of fluid per dose. Higher concentrations (e.g., 10 mg/mL) may produce phlebitis or inflammation at the injection site upon inadvertent extravasation. Standard, commercially available electrolyte and glucose solutions are suitable for intravenous administration; biologic or colloidal fluids (e.g., blood products, protein solutions, etc.) are not recommended.

Once diluted for administration, each dose should be used within 24 hours.

Parenteral drug products should be inspected visually for particulate matter and discoloration prior to administration, whenever solution and container permit.

HOW SUPPLIED:

Acyclovir Injection, USP equivalent to acyclovir is available:

Product Code | Unit of Sale | Strength | Each
622010 | NDC 65219-622-10 Unit of 10 | 500 mg per 10 mL (50 mg per mL) | NDC 65219-622-02 In a 10 mL clear, tubular glass vial
622020 | NDC 65219-624-20 Unit of 10 | 1,000 mg per 20 mL (50 mg per mL) | NDC 65219-624-04 In a 20 mL clear, tubular glass vial

Store at 20°C to 25°C (68°F to 77°F)[see USP Controlled Room Temperature].

Discard unused portion.

The container closure is not made with natural rubber latex.

Manufactured for:

Lake Zurich, IL 60047
www.fresenius-kabi.com/us
451815
June 2024
Made in India
LEIA-301.00

PACKAGE LABEL

PACKAGE LABEL - PRINCIPAL DISPLAY - Acyclovir 10 mL Single Dose Vial Label

NDC 65219-622-02 622010

Acyclovir

Injection, USP

500 mg per 10 mL*

(50 mg per mL)

For IV Infusion Only

MUST BE DILUTED PRIOR TO USE

Rx only

10 mL Single Dose Vial

PACKAGE LABEL

PACKAGE LABEL - PRINCIPAL DISPLAY - Acyclovir 10 mL Single Dose Vial Tray Label

NDC 65219-622-10 622010

Acyclovir

Injection, USP

500 mg per 10 mL*

(50 mg per mL)

For IV Infusion Only

MUST BE DILUTED PRIOR TO USE

Rx only

10 x 10 mL Single Dose Vials

PACKAGE LABEL - PRINCIPAL DISPLAY - Acyclovir 20 mL Single Dose Vial Label

NDC 65219-624-04 622020

Acyclovir

Injection, USP

1,000 mg per 20 mL*

(50 mg per mL)

For IV Infusion Only

MUST BE DILUTED PRIOR TO USE

Rx only

20 mL Single Dose Vial

PACKAGE LABEL - PRINCIPAL DISPLAY - Acyclovir 20 mL Single Dose Carton

NDC 65219-624-20 622020

Acyclovir

Injection, USP

1,000 mg per 20 mL*

(50 mg per mL)

For IV Infusion Only

MUST BE DILUTED PRIOR TO USE

Rx only

10 x 20 mL Single Dose Vials